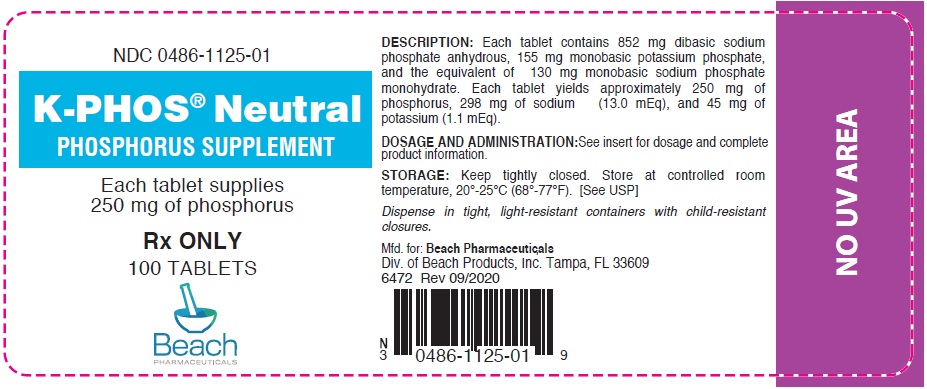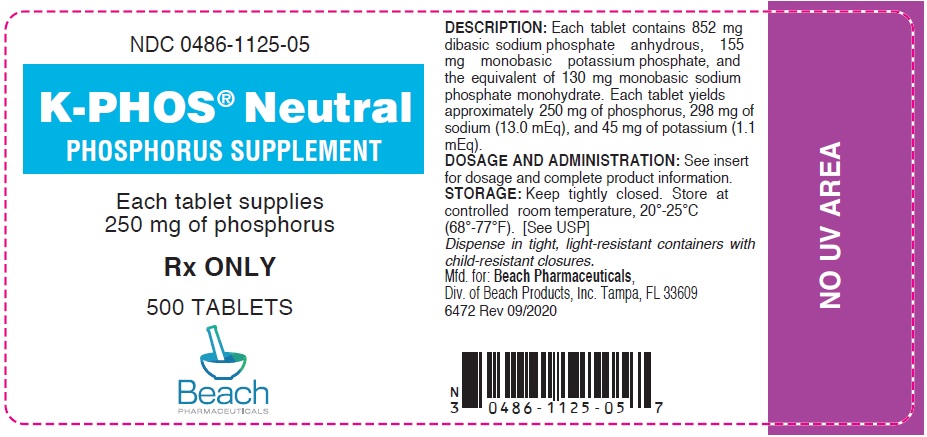 DRUG LABEL: K Phos

NDC: 0486-1125 | Form: TABLET, COATED
Manufacturer: Beach Products, Inc.
Category: prescription | Type: HUMAN PRESCRIPTION DRUG LABEL
Date: 20230223

ACTIVE INGREDIENTS: SODIUM PHOSPHATE, DIBASIC, ANHYDROUS 852 mg/1 1; POTASSIUM PHOSPHATE, MONOBASIC 155 mg/1 1; SODIUM PHOSPHATE, MONOBASIC, MONOHYDRATE 130 mg/1 1
INACTIVE INGREDIENTS: POVIDONE K29/32; LACTOSE MONOHYDRATE; SODIUM STARCH GLYCOLATE TYPE A POTATO; MAGNESIUM STEARATE; STEARIC ACID; HYPROMELLOSES; SODIUM CITRATE; MALTODEXTRIN; TRIACETIN; TITANIUM DIOXIDE; POLYETHYLENE GLYCOL

K-PHOS® NEUTRAL
Phosphorus Supplement

Rx ONLY

DESCRIPTION

Each tablet contains 852 mg dibasic sodium phosphate anhydrous, 155 mg monobasic potassium phosphate, and the equivalent of 130 mg monobasic sodium phosphate monohydrate. Each tablet yields approximately 250 mg of phosphorus, 298 mg of sodium (13.0 mEq) and 45 mg of potassium (1.1 mEq). The components of K-PHOS® NEUTRAL have the following chemical names and molecular formulae:

Dibasic Sodium Phosphate, Anhydrous
Molecular Formula: Na2HPO4, Molecular Weight: 141.96.

Monobasic Potassium Phosphate
Molecular Formula: KH2PO4, Molecular Weight: 136.09.

Monobasic Sodium Phosphate, Monohydrate
Molecular Formula:NaH2PO4.H2O, Molecular Weight: 137.98.

Inactive Ingredients: Lactose monohydrate, povidone, white coating (hydroxypropyl methylcellulose, titanium dioxide, maltodextrin, triacetin, glycerol triacetate, polyethylene glycol, sodium citrate, and stearic acid), sodium starch glycolate, and magnesium stearate.

CLINICAL PHARMACOLOGY

Phosphorus has a number of important functions in the biochemistry of the body. The bulk of the body's phosphorus is located in the bones, where it plays a key role in osteoblastic and osteoclastic activities. Enzymatically catalyzed phosphate-transfer reactions are numerous and vital in the metabolism of carbohydrate, lipid and protein, and a proper concentration of the anion is of primary importance in assuring an orderly biochemical sequence. In addition, phosphorus plays an important role in modifying steady-state tissue concentrations of calcium. Phosphate ions are important buffers of the intracellular fluid, and also play a primary role in the renal excretion of hydrogen ion.

Oral administration of inorganic phosphates increases serum phosphate levels. Phosphates lower urinary calcium levels in idiopathic hypercalciuria.

In general, in adults, about two thirds of the ingested phosphate is absorbed from the bowel, most of which is rapidly excreted into the urine.

INDICATIONS AND USAGE

K-PHOS® NEUTRAL increases urinary phosphate and pyrophosphate. As a phosphorus supplement, each tablet supplies 25% of the U.S. Recommended Daily Allowance (U.S.RDA) of phosphorus for adul t s and children over 4 years of age.

CONTRAINDICATIONS

This product is contraindicated in patients with infected phosphate stones, in patients with severely impaired renal function (less than 30% of normal) and in the presence of hyperphosphatemia.

PRECAUTIONS

General

This product contains potassium and sodium and should be used with caution if regulation of these elements is desired. Occasionally, some individuals may experience a mild laxative effect during the first few days of phosphate therapy. If laxation persists to an unpleasant degree, reduce the daily dosage until this effect subsides or, if necessary, discontinue the use of this product.

Caution should be exercised when prescribing this product in the following conditions: Cardiac disease (particularly in digitalized patients); severe adrenal insufficiency (Addison's disease); acute dehydration; severe renal insufficiency; renal function impairment or chronic renal disease; extensive tissue breakdown (such as severe burns); myotonia congenita; cardiac failure; cirrhosis of the liver or severe hepatic disease; peripheral or pulmonary edema; hypernatremia; hypertension; toxemia of pregnancy; hypoparathyroidism; and acute pancreatitis. Rickets may benefit from phosphate therapy, but caution should be exercised. High serum phosphate levels may increase the incidence of extra-skeletal calcification.

Information for Patients

Patients with kidney stones may pass old stones when phosphate therapy is started and should be warned of this possibility. Patients should be advised to avoid the use of antacids containing aluminum, magnesium, or calcium which may prevent the absorption of phosphate.

Laboratory Tests

Careful monitoring of renal function and serum calcium, phosphorus, potassium and sodium may be required at periodic intervals during phosphate therapy. Other tests may be warranted in some patients, depending on conditions.

Drug Interactions

The use of antacids containing magnesium, aluminum, or calcium in conjunction with phosphate preparations may bind the phosphate and prevent its absorption. Concurrent use of antihypertensives, especially diazoxide, guanethidine, hydralazine, methyldopa, or rauwolfia alkaloid; or corticosteroids, especially mineralocorticoids or corticotropin, with sodium phosphate may result in hypernatremia. Calciumcontaining preparations and/or Vitamin D may antagonize the effects of phosphates in the treatment of hypercalcemia. Potassium-containing medications or potassium-sparingdiuretics may cause hyperkalemia. Patients should have serum potassium level determinations at periodic intervals.

Carcinogenesis, Mutagenesis, Impairment of Fertility

No long-term or reproduction studies in animals or humans have been performed with K-PHOS ® NEUTRAL to evaluate its carcinogenic, mutagenic, or impairment of fertility potential.

Pregnancy

Teratogenic Effects

Pregnancy Category C

Animal reproduction studies have not been conducted with K-PHOS® NEUTRAL. It is also not known whether this product can cause fetal harm when administered to a pregnant woman or can affect reproductive capacity. This product should be given to a pregnant woman only if clearly needed.

Nursing Mothers

It is not known whether this drug is excreted in human milk. Because many drugs are excreted in human milk, caution should be exercised when this product is administered to a nursing woman.

Pediatric Use

See DOSAGE AND ADMINISTRATION

ADVERSE REACTIONS

Gastrointestinal upset (diarrhea, nausea, stomach pain and vomiting) may occur with phosphate therapy. Also, bone and joint pain (possible phosphate-induced osteomalacia) could occur. The following adverse effects may be observed (primarily from sodium or potassium): headaches; dizziness; mental confusion; seizures; weakness or heaviness of legs; unusual tiredness or weakness; muscle cramps; numbness, tingling, pain, or weakness of hands or feet; numbness or tingling around lips; fast or irregular heartbeat; shortness of breath or troubled breathing; swelling of feet or lower legs; unusual weight gain; low urine output; unusual thirst.

DOSAGE AND ADMINISTRATION

K-PHOS® NEUTRAL tablets should be taken with a full glass of water, with meals and at bedtime. Adults: One or two tablets four times daily; Pediatric Patients over 4 years of age: One tablet four times daily. For Pediatric Patients under 4 years of age, use only as directed by a physician.

HOW SUPPLIED

White, film coated, scored capsule-shaped tablet with the name BEACH and the number 1125 imprinted on each tablet. Bottles of 100 (NDC 0486-1125-01) and bottles of 500 (NDC 0486-1125-05) tablets.

STORAGE

Keep tightly closed. Store at controlled room temperature, 20°-25°C (68°-77°F). [See USP]

Dispense in tight, light-resistant containers with child-resistant closures.

Manufactured for: BEACH PHARMACEUTICALS, Div. of Beach Products, Inc., Tampa, FL 33609

6472 Rev 09/2020

PRINCIPAL DISPLAY PANEL - 250 mg Tablet Bottle Label

NDC 0486-1125-01

K-PHOS® Neutral
PHOSPHORUS SUPPLEMENT

Each tablet supplies
250 mg of phosphorus

Rx ONLY

100 TABLETS

Beach
PHARMACEUTICALS

PRINCIPAL DISPLAY PANEL - 250 mg Tablet Bottle Label

NDC 0486-1125-05

K-PHOS® Neutral
PHOSPHORUS SUPPLEMENT

Each tablet supplies
250 mg of phosphorus

Rx ONLY

500 TABLETS

Beach
PHARMACEUTICALS